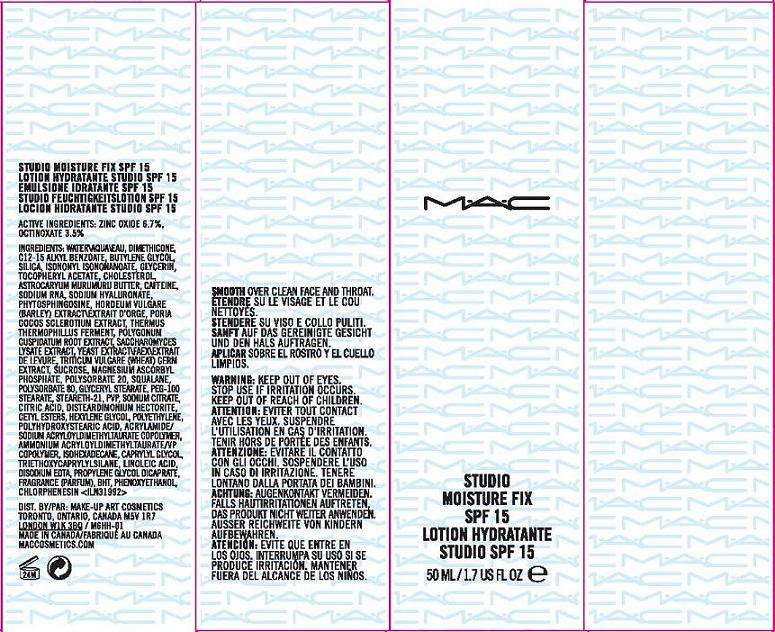 DRUG LABEL: STUDIO MOISTURE FIX
NDC: 40046-0046 | Form: LOTION
Manufacturer: MAKE UP ART COSMETICS
Category: otc | Type: HUMAN OTC DRUG LABEL
Date: 20110715

ACTIVE INGREDIENTS: ZINC OXIDE 6.7 mL/100 mL; OCTINOXATE 3.5 mL/100 mL
INACTIVE INGREDIENTS: WATER; DIMETHICONE; ALKYL (C12-15) BENZOATE; BUTYLENE GLYCOL; SILICON DIOXIDE; ISONONYL ISONONANOATE; GLYCERIN; ALPHA-TOCOPHEROL ACETATE; CHOLESTEROL; ASTROCARYUM MURUMURU SEED BUTTER; CAFFEINE; HYALURONATE SODIUM; BARLEY; FU LING; POLYGONUM CUSPIDATUM ROOT; SACCHAROMYCES CEREVISIAE; YEAST; WHEAT GERM; SUCROSE; MAGNESIUM ASCORBYL PHOSPHATE; POLYSORBATE 20; SQUALANE; POLYSORBATE 80; GLYCERYL MONOSTEARATE; PEG-100 STEARATE; STEARETH-21; POVIDONE K17; SODIUM CITRATE; CITRIC ACID MONOHYDRATE; CETYL ESTERS WAX; HEXYLENE GLYCOL; POLYHYDROXYSTEARIC ACID (2300 MW); ISOHEXADECANE; CAPRYLYL GLYCOL; TRIETHOXYCAPRYLYLSILANE; LINOLEIC ACID; EDETATE DISODIUM; PROPYLENE GLYCOL DICAPRATE; BUTYLATED HYDROXYTOLUENE; PHENOXYETHANOL; CHLORPHENESIN

ACTIVE INGREDIENT

ACTIVE INGREDIENTS: ZINC OXIDE 6.70% [] OCTINOXATE 3.50%

INACTIVE INGREDIENT

INACTIVE INGREDIENTS: WATER [] DIMETHICONE [] C12-15 ALKYL BENZOATE [] BUTYLENE GLYCOL [] SILICA [] ISONONYL ISONONANOATE [] GLYCERIN [] TOCOPHERYL ACETATE [] CHOLESTEROL [] ASTROCARYUM MURUMURU BUTTER [] CAFFEINE [] SODIUM RNA [] SODIUM HYALURONATE [] PHYTOSPHINGOSINE [] HORDEUM VULGARE (BARLEY) EXTRACT\EXTRAIT D'ORGE [] PORIA COCOS SCLEROTIUM EXTRACT [] THERMUS THERMOPHILLUS FERMENT [] POLYGONUM CUSPIDATUM ROOT EXTRACT [] SACCHAROMYCES LYSATE EXTRACT [] YEAST EXTRACT\FAEX\EXTRAIT DE LEVURE [] TRITICUM VULGARE (WHEAT) GERM EXTRACT [] SUCROSE [] MAGNESIUM ASCORBYL PHOSPHATE [] POLYSORBATE 20 [] SQUALANE [] POLYSORBATE 80 [] GLYCERYL STEARATE [] PEG-100 STEARATE [] STEARETH-21 [] PVP [] SODIUM CITRATE [] CITRIC ACID [] DISTEARDIMONIUM HECTORITE [] CETYL ESTERS [] HEXYLENE GLYCOL [] POLYETHYLENE [] POLYHYDROXYSTEARIC ACID [] ACRYLAMIDE/SODIUM ACRYLOYLDIMETHYLTAURATE COPOLYMER [] AMMONIUM ACRYLOYLDIMETHYLTAURATE/VP COPOLYMER [] ISOHEXADECANE [] CAPRYLYL GLYCOL [] TRIETHOXYCAPRYLYLSILANE [] LINOLEIC ACID [] DISODIUM EDTA [] PROPYLENE GLYCOL DICAPRATE [] FRAGRANCE (PARFUM) [] BHT [] PHENOXYETHANOL [] CHLORPHENESIN

WHEN USING

DIRECTIONS: SMOOTH OVER CLEAN FACE AND THROAT

WARNINGS

WARNING: KEEP OUT OF EYES. STOP USE IF IRRITATION OCCURS. KEEP OUT OF REACH OF CHILDREN.

PACKAGE LABEL

PRINICIPAL DISPLAY PANEL

MAC

STUDIO

MOISTURE FIX

SPF 15

1.7 US FL OZ/ 50 ML

DISTR MAKE-UP ART COSMETICS

TORONTO, ONTARIO, CANADA, M5V1R7